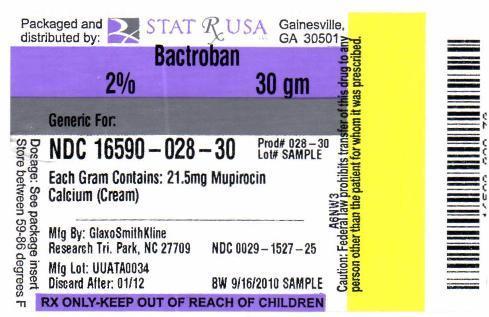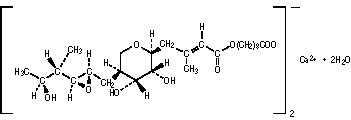 DRUG LABEL: BACTROBAN
NDC: 16590-028 | Form: CREAM
Manufacturer: STAT RX USA LLC
Category: prescription | Type: HUMAN PRESCRIPTION DRUG LABEL
Date: 20110106

ACTIVE INGREDIENTS: MUPIROCIN CALCIUM 20 mg/1 g
INACTIVE INGREDIENTS: BENZYL ALCOHOL; CETETH-20; CETYL ALCOHOL; MINERAL OIL; PHENOXYETHANOL; WATER; STEARYL ALCOHOL; XANTHAN GUM

BACTROBAN CREAM®
(mupirocin calcium cream, 2%)
For Dermatologic Use

DESCRIPTION

BACTROBAN CREAM (mupirocin calcium cream, 2%) contains the dihydrate crystalline calcium hemi-salt of the antibiotic mupirocin. Chemically, it is (αE,2S,3R,4R,5S)-5-[(2S,3S,4S,5S)-2,3-Epoxy-5-hydroxy-4-methylhexyl]tetrahydro-3,4-dihydroxy-β-methyl-2H-pyran-2-crotonic acid, ester with 9-hydroxynonanoic acid, calcium salt (2:1), dihydrate.

The molecular formula of mupirocin calcium is (C26H43O9)2Ca•2H2O, and the molecular weight is 1075.3. The molecular weight of mupirocin free acid is 500.6. The structural formula of mupirocin calcium is:

BACTROBAN CREAM is a white cream that contains 2.15% w/w mupirocin calcium (equivalent to 2.0% mupirocin free acid) in an oil and water-based emulsion. The inactive ingredients are benzyl alcohol, cetomacrogol 1000, cetyl alcohol, mineral oil, phenoxyethanol, purified water, stearyl alcohol, and xanthan gum.

CLINICAL PHARMACOLOGY

Pharmacokinetics

Systemic absorption of mupirocin through intact human skin is minimal. The systemic absorption of mupirocin was studied following application of BACTROBAN CREAM 3 times daily for 5 days to various skin lesions (>10 cm in length or 100 cm^2 in area) in 16 adults (aged 29 to 60 years) and 10 children (aged 3 to 12 years). Some systemic absorption was observed as evidenced by the detection of the metabolite, monic acid, in urine. Data from this study indicated more frequent occurrence of percutaneous absorption in children (90% of patients) compared to adults (44% of patients); however, the observed urinary concentrations in children (0.07 - 1.3 mcg/mL [1 pediatric patient had no detectable level]) are within the observed range (0.08 - 10.03 mcg/mL [9 adults had no detectable level]) in the adult population. In general, the degree of percutaneous absorption following multiple dosing appears to be minimal in adults and children. Any mupirocin reaching the systemic circulation is rapidly metabolized, predominantly to inactive monic acid, which is eliminated by renal excretion.

Microbiology

Mupirocin is an antibacterial agent produced by fermentation using the organism Pseudomonas fluorescens. It is active against a wide range of gram-positive bacteria including methicillin-resistant Staphylococcus aureus (MRSA). It is also active against certain gram-negative bacteria. Mupirocin inhibits bacterial protein synthesis by reversibly and specifically binding to bacterial isoleucyl transfer-RNA synthetase. Due to this unique mode of action, mupirocin demonstrates no in vitro cross-resistance with other classes of antimicrobial agents.

Resistance occurs rarely; however, when mupirocin resistance does occur, it appears to result from the production of a modified isoleucyl-tRNA synthetase. High-level plasmid-mediated resistance (MIC >1024 mcg/mL) has been reported in some strains of Staphylococcus aureus and coagulase-negative staphylococci.

Mupirocin is bactericidal at concentrations achieved by topical application. The minimum bactericidal concentration (MBC) against relevant pathogens is generally 8-fold to 30-fold higher than the minimum inhibitory concentration (MIC). In addition, mupirocin is highly protein bound (>97%), and the effect of wound secretions on the MICs of mupirocin has not been determined.

Mupirocin has been shown to be active against most strains of S. aureus and Streptococcus pyogenes, both in vitro and in clinical studies. (See INDICATIONS AND USAGE.) The following in vitro data are available, BUT THEIR CLINICAL SIGNIFICANCE IS UNKNOWN. Mupirocin is active against most strains of Staphylococcus epidermidis and Staphylococcus saprophyticus.

INDICATIONS AND USAGE

BACTROBAN CREAM is indicated for the treatment of secondarily infected traumatic skin lesions (up to 10 cm in length or 100 cm^2 in area) due to susceptible strains of S. aureus and S. pyogenes.

CONTRAINDICATIONS

BACTROBAN CREAM is contraindicated in patients with known hypersensitivity to any of the constituents of the product.

WARNINGS

Avoid contact with the eyes.

In the event of a sensitization or severe local irritation from BACTROBAN CREAM, usage should be discontinued, and appropriate alternative therapy for the infection instituted.

PRECAUTIONS

General

As with other antibacterial products, prolonged use may result in overgrowth of nonsusceptible microorganisms, including fungi. (See DOSAGE AND ADMINISTRATION.)

BACTROBAN CREAM is not formulated for use on mucosal surfaces.

Information for Patients

• Use this medication only as directed by your healthcare provider. It is for external use only. Avoid contact with the eyes.

• The treated area may be covered by gauze dressing if desired.

• Report to your healthcare provider any signs of local adverse reactions. The medication should be stopped and your healthcare provider contacted if irritation, severe itching, or rash occurs.

• If no improvement is seen in 3 to 5 days, contact your healthcare provider.

Drug Interactions

The effect of the concurrent application of topical mupirocin calcium cream and other topical products has not been studied.

Carcinogenesis, Mutagenesis, Impairment of Fertility

Long-term studies in animals to evaluate carcinogenic potential of mupirocin calcium have not been conducted.

Results of the following studies performed with mupirocin calcium or mupirocin sodium in vitro and in vivo did not indicate a potential for mutagenicity: Rat primary hepatocyte unscheduled DNA synthesis, sediment analysis for DNA strand breaks, Salmonella reversion test (Ames), Escherichia coli mutation assay, metaphase analysis of human lymphocytes, mouse lymphoma assay, and bone marrow micronuclei assay in mice.

Fertility studies were performed in rats with mupirocin administered subcutaneously at doses up to 49 times a human topical dose of 1 gram/day (approximately 20 mg mupirocin per day) on a mg/m^2 basis and revealed no evidence of impaired fertility from mupirocin sodium.

Pregnancy

TERATOGENIC EFFECTS

Teratogenic Effects: Pregnancy Category B. Teratology studies have been performed in rats and rabbits with mupirocin administered subcutaneously at doses up to 78 and 154 times, respectively, a human topical dose of 1 gram/day (approximately 20 mg mupirocin per day) on a mg/m^2 basis and revealed no evidence of harm to the fetus due to mupirocin. There are, however, no adequate and well-controlled studies in pregnant women. Because animal reproduction studies are not always predictive of human response, this drug should be used during pregnancy only if clearly needed.

Nursing Mothers

It is not known whether this drug is excreted in human milk. Because many drugs are excreted in human milk, caution should be exercised when BACTROBAN CREAM is administered to a nursing woman.

Pediatric Use

The safety and effectiveness of BACTROBAN CREAM have been established in the age groups 3 months to 16 years. Use of BACTROBAN CREAM in these age groups is supported by evidence from adequate and well-controlled studies of BACTROBAN CREAM in adults with additional data from 93 pediatric patients studied as part of the pivotal trials in adults. (See CLINICAL STUDIES.)

Geriatric Use

In 2 well-controlled studies, 30 patients older than 65 years were treated with BACTROBAN CREAM. No overall difference in the efficacy or safety of BACTROBAN CREAM was observed in this patient population when compared to that observed in younger patients.

ADVERSE REACTIONS

In 2 randomized, double-blind, double-dummy trials, 339 patients were treated with topical BACTROBAN CREAM plus oral placebo. Adverse events thought to be possibly or probably drug-related occurred in 28 (8.3%) patients. The incidence of those events that were reported in at least 1% of patients enrolled in these trials were: Headache (1.7%), rash, and nausea (1.1% each).

Other adverse events thought to be possibly or probably drug-related which occurred in less than 1% of patients were: Abdominal pain, burning at application site, cellulitis, dermatitis, dizziness, pruritus, secondary wound infection, and ulcerative stomatitis.

In a supportive study in the treatment of secondarily infected eczema, 82 patients were treated with BACTROBAN CREAM. The incidence of adverse events thought to be possibly or probably drug-related was as follows: Nausea (4.9%), headache, and burning at application site (3.6% each), pruritus (2.4%) and 1 report each of abdominal pain, bleeding secondary to eczema, pain secondary to eczema, hives, dry skin, and rash.

OVERDOSAGE

Intravenous infusions of 252 mg, as well as single oral doses of 500 mg of mupirocin, have been well tolerated in healthy adult subjects. There is no information regarding overdose of BACTROBAN CREAM.

DOSAGE AND ADMINISTRATION

A small amount of BACTROBAN CREAM should be applied to the affected area 3 times daily for 10 days. The area treated may be covered with gauze dressing if desired. Patients not showing a clinical response within 3 to 5 days should be re-evaluated.

CLINICAL STUDIES

The efficacy of topical BACTROBAN CREAM for the treatment of secondarily infected traumatic skin lesions (e.g., lacerations, sutured wounds, and abrasions not more than 10 cm in length or 100 cm^2 in total area) was compared to that of oral cephalexin in 2 randomized, double-blind, double-dummy clinical trials. Clinical efficacy rates at follow-up in the per protocol populations (adults and pediatric patients included) were 96.1% for BACTROBAN CREAM (n = 231) and 93.1% for oral cephalexin (n = 219). Pathogen eradication rates at follow-up in the per protocol populations were 100% for both BACTROBAN CREAM and oral cephalexin.

Pediatrics: There were 93 pediatric patients aged 2 weeks to 16 years enrolled per protocol in the secondarily infected skin lesion studies, although only 3 were less than 2 years of age in the population treated with BACTROBAN CREAM. Patients were randomized to either 10 days of topical BACTROBAN CREAM 3 times daily or 10 days of oral cephalexin (250 mg 4 times daily for patients >40 kg or 25 mg/kg/day oral suspension in 4 divided doses for patients ≤40 kg). Clinical efficacy at follow-up (7 to 12 days post-therapy) in the per protocol populations was 97.7% (43/44) for BACTROBAN CREAM and 93.9% (46/49) for cephalexin. Only 1 adverse event (headache) was thought to be possibly or probably related to drug therapy with BACTROBAN CREAM in the intent-to-treat pediatric population of 70 children (1.4%).

HOW SUPPLIED

BACTROBAN CREAM is supplied in 15-gram and 30-gram tubes.

NDC 0029-1527-22 (15-gram tube)

NDC 0029-1527-25 (30-gram tube)

Store at or below 25°C (77°F). Do not freeze.

GlaxoSmithKline

Research Triangle Park, NC 27709

BACTROBAN CREAM is a registered trademark of GlaxoSmithKline.

©2005, GlaxoSmithKline. All rights reserved.

May 2005 BB:L7B